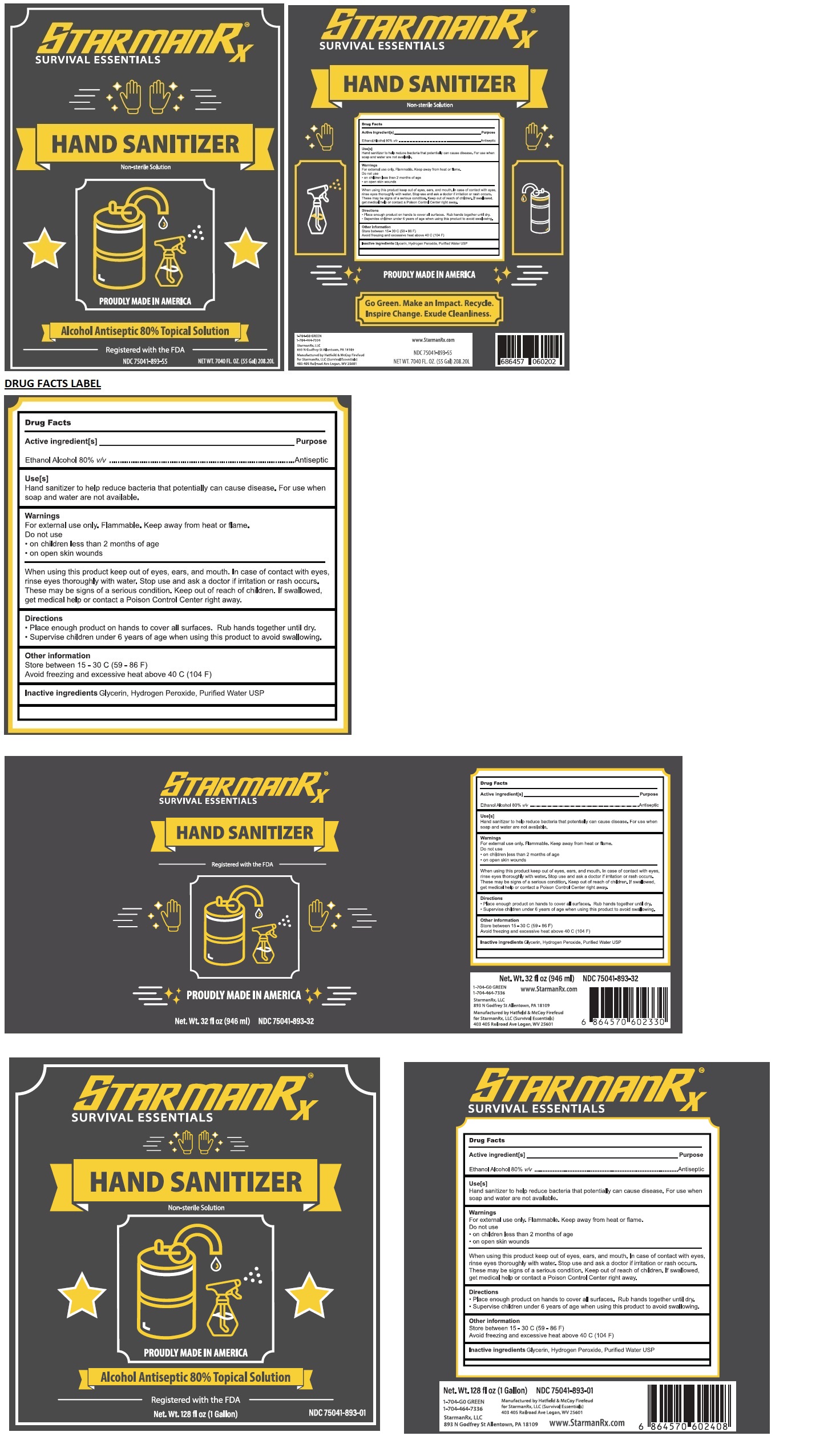 DRUG LABEL: STARMANRX SURVIVAL ESSENTIALS HAND SANITIZER
NDC: 75041-893 | Form: SOLUTION
Manufacturer: STARMANRX LLC
Category: otc | Type: HUMAN OTC DRUG LABEL
Date: 20201229

ACTIVE INGREDIENTS: ALCOHOL 80 L/100 L
INACTIVE INGREDIENTS: GLYCERIN; HYDROGEN PEROXIDE; WATER

StarmanRx Survival Essentials Hand Sanitizer

Active ingredient[s]

Ethanol Alcohol 80% v/v

Purpose

Antiseptic

Use[s]

Hand Sanitizer to help reduce bacteria that potentially can cause disease. For use when soap and water are not available.

Warnings

For external use only. Flammable. Keep away from heat or flame.
Do not use
• on children less than 2 months of age
• on open skin wounds
When using this product keep out of eyes, ears, and mouth. In case of contact with eyes, rinse eyes thoroughly with water.
Stop use and ask a doctor if irritation or rash occurs. These may be signs of a serious condition.

Keep out of reach of children. If swallowed, get medical help or contact a Poison Control Center right away.

Directions

• Place enough product on hands to cover all surfaces. Rub hands together until dry.
• Supervise children under 6 years of age when using this product to avoid swallowing.

Other Information

Store between 15 - 30 C (59 - 86 F)
Avoid freezing and excessive heat above 40 C (104 F)

Inactive ingredients

Glycerin, Hydrogen peroxide, Purified Water USP

Non-sterile Solution

PROUDLY MADE IN AMERICA

Alcohol Antiseptic 80% Topical Solution

Registered with the FDA

Go Green. Make an Impact. Recycle.

Inspire Change. Exude Cleanliness.

StarmanRx, LLC

893 N Godfrey St Allentown, PA 18109

Manufactured by Hatfield & McCoy FireFeud

for StarmanRx, LLC (Survival Essentials)

403 405 Railroad Ave Logan, WV 25601

www.StarmanRx.com